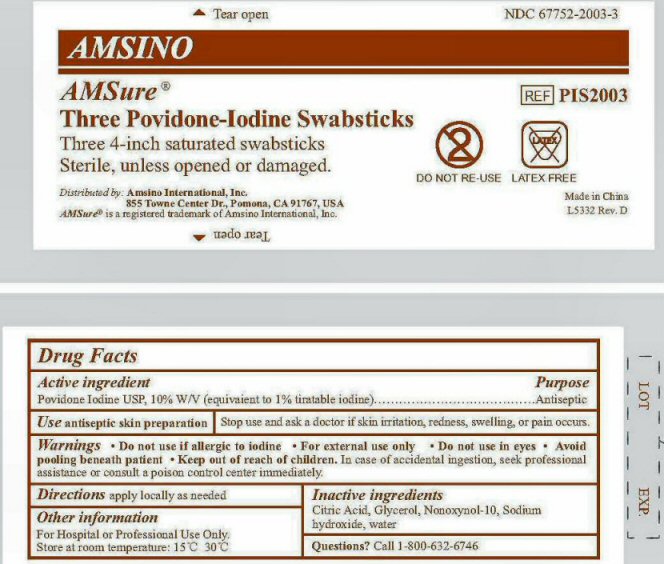 DRUG LABEL: AMSure  
NDC: 67752-2003 | Form: SWAB
Manufacturer: Amsino International, Inc.
Category: otc | Type: HUMAN OTC DRUG LABEL
Date: 20120202

ACTIVE INGREDIENTS: Povidone-Iodine 0.1 mg/1 mL
INACTIVE INGREDIENTS: CITRIC ACID MONOHYDRATE; GLYCERIN; NONOXYNOL-10; SODIUM HYDROXIDE; WATER

Active Ingredient Section

Active ingredient
Povidone Iodine USP, 10% W/V (equivaient to 1% tiratable iodine)

Purpose Section

Purpose Antiseptic

Stop Use Section

Stop use and ask a doctor if skin irritation, redness, swelling, or pain occurs.

Warnings Section

Warnings • Do not use if allergic to iodine • For external use only • Do not use in eyes • Avoid
pooling beneath patient • In case of accidental ingestion, seek professional
assistance or consult a poison control center immediately.

Keep Out of Reach of Children Section

Keep out of reach of children.

Indications and Uses Section

Uses antiseptic skin preparation

Directions Section

Directions apply locally as needed

Inactive Ingredients Section

Inactive ingredients
Citric Acid, Glycerol, Nonoxynol-10, Sodium hydroxide, water

Questions Section

Questions? Call 1-800-632-6746

Other Information Section

Other information

For Hospital or Professional Use Only.

Store at room temperature: 15oC - 30oC

Package Label

AMSINO AMSure Three Povidone-Iodine Swabsticks NDC 67752-2003-3 REF PIS2003
Three 4-inch saturated swabsticks Sterile, unless opened or damaged DO NOT RE-USE LATEX-FREE
Distributed by: Amsion International, inc. 855 Towne Center Dr., Pomona, CA 91757, USA AMSure is a registered trademark of Amsino International, Inc. Made in China L5332 Rev. D
Tear open LOT EXP.